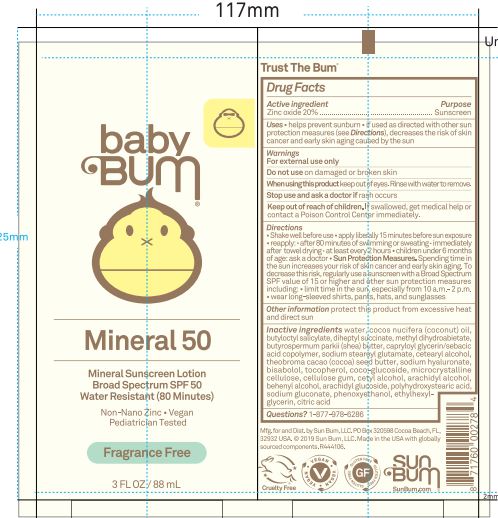 DRUG LABEL: Baby Bum Mineral 50 Sunscreen
NDC: 69039-686 | Form: LOTION
Manufacturer: Sun Bum LLC
Category: otc | Type: HUMAN OTC DRUG LABEL
Date: 20250822

ACTIVE INGREDIENTS: ZINC OXIDE 200 mg/1 mL
INACTIVE INGREDIENTS: METHYL DIHYDROABIETATE; ARACHIDYL ALCOHOL; PHENOXYETHANOL; WATER; COCONUT OIL; DIHEPTYL SUCCINATE; CETEARYL ALCOHOL; THEOBROMA CACAO (COCOA) SEED BUTTER; SODIUM HYALURONATE; MICROCRYSTALLINE CELLULOSE; POLYHYDROXYSTEARIC ACID (2300 MW); BUTYLOCTYL SALICYLATE; SHEA BUTTER; BISABOLOL; ETHYLHEXYLGLYCERIN; SODIUM STEAROYL GLUTAMATE; TOCOPHEROL; ARACHIDYL GLUCOSIDE; BEHENYL ALCOHOL; CAPRYLOYL GLYCERIN/SEBACIC ACID COPOLYMER (2000 MPA.S); COCO-GLUCOSIDE; CELLULOSE GUM; CETYL ALCOHOL; SODIUM GLUCONATE; CITRIC ACID

Baby Bum Mineral 50 Sunscreen Lotion

Active Ingredient

Zinc Oxide 20%

Purpose

Sunscreen

Uses

• helps prevent sunburn • if used as directed with other sun protection measures, (see Directions) decreases the risk of skin cancer and early skin aging caused by the sun

Warnings

For external use only.

Do not use on damaged or broken skin

When using this product keep out of eyes. Rinse with water to remove.

Stop use and ask a doctor if rash occurs

Keep out of reach of children. If swallowed, get medical help or contact a Poison Control Center immediately.

Warnings

Keep Out Of Reach Of Children

Directions

• shake well before use

• apply liberally 15 minutes before sun exposure

• reapply: • after 80 minutes of swimming or sweating • immediately after towel drying • at least every 2 hours

• children under 6 months of age: ask a doctor

• Sun Protection Measures. Spending time in the sun increases your risk of skin cancer and early skin aging. To decrease this risk, regularly use a sunscreen with a Broad Spectrum SPF value of 15 or higher and other sun protection measures including:

• limit time in the sun, especially from 10 a.m.- 2 p.m.

• wear long-sleeved shirts, pants, hats and sunglasses

Directions

• shake well before use

• apply liberally 15 minutes before sun exposure

Other Information

protect this product from excessive heat and direct sun

Inactive Ingredients

Water, Cocos Nucifera (Coconut) Oil, Butyloctyl Salicylate, Diheptyl Succinate, Methyl Dihydroabietate, Butyrospermum Parkii (Shea Butter), Capryloyl Glycerin/Sebacic Acid Copolymer, Sodium Stearoyl Glutamate, Cetearyl Alcohol, Theobroma Cacao (Cocoa) Seed Butter, Sodium Hyaluronate, Bisabolol, Tocopherol, Coco-Glucoside, Microcrystalline Cellulose, Cellulose Gum, Cetyl Alcohol, Arachidyl Alcohol, Behenyl Alcohol, Arachidyl Glucoside, Polyhydroxystearic Acid, Sodium Gluconate, Phenoxyethanol, Ethylhexylglycerin, Citric Acid

Questions?

1-877-978-6286